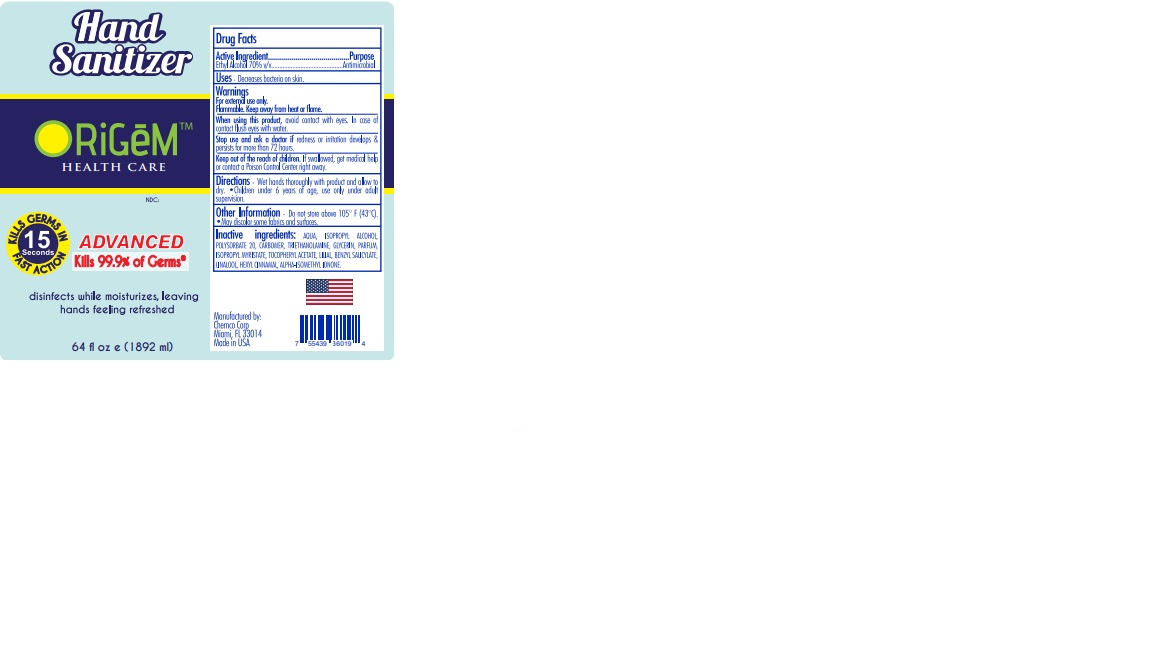 DRUG LABEL: Ethyl Alcohol
NDC: 49283-700 | Form: GEL
Manufacturer: Chemco Corporation
Category: otc | Type: HUMAN OTC DRUG LABEL
Date: 20200908

ACTIVE INGREDIENTS: ALCOHOL 70 mL/100 mL
INACTIVE INGREDIENTS: .ALPHA.-HEXYLCINNAMALDEHYDE; BUTYLPHENYL METHYLPROPIONAL; ISOMETHYL-.ALPHA.-IONONE; WATER; GLYCERIN; POLYSORBATE 20; CARBOMER 940; TROLAMINE; ISOPROPYL MYRISTATE; ALPHA-TOCOPHEROL ACETATE; BENZYL SALICYLATE; LINALOOL, (+/-)-

49283-700-64